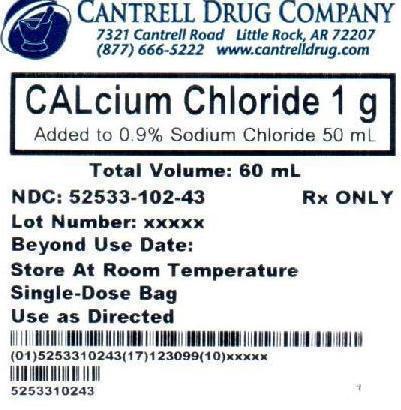 DRUG LABEL: Calcium Chloride
NDC: 52533-102 | Form: INJECTION, SOLUTION
Manufacturer: Cantrell Drug Company
Category: prescription | Type: HUMAN PRESCRIPTION DRUG LABEL
Date: 20121024

ACTIVE INGREDIENTS: CALCIUM CHLORIDE 20 mg/1 mL
INACTIVE INGREDIENTS: Sodium Chloride 9 mg/1 mL; Water

Calcium Chloride 1 g Added to 0.9% Sodium Chloride 50 mL Bag